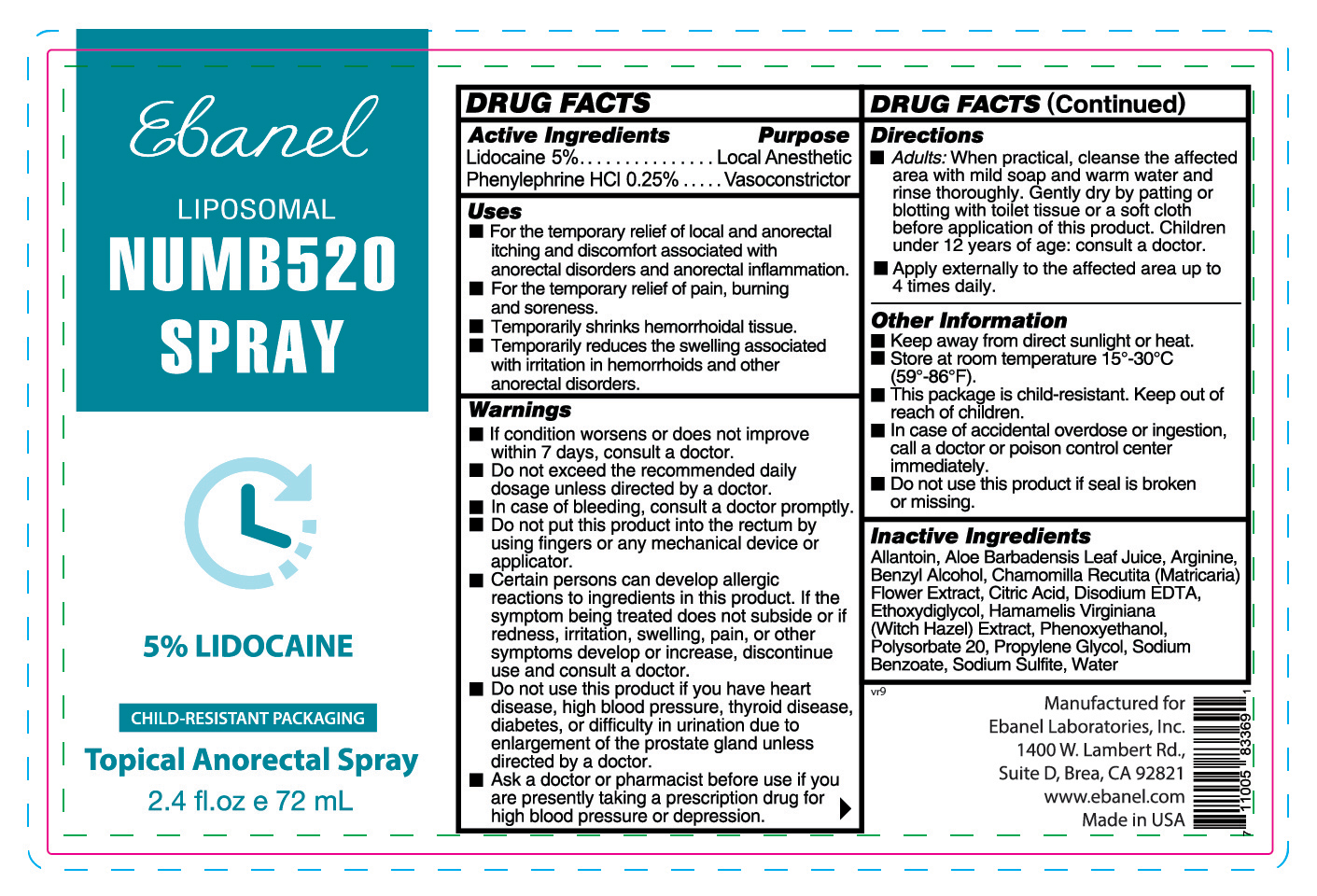 DRUG LABEL: Numb520Spray
NDC: 72654-037 | Form: LIQUID
Manufacturer: Ebanel Laboratories, Inc.
Category: otc | Type: HUMAN OTC DRUG LABEL
Date: 20250527

ACTIVE INGREDIENTS: LIDOCAINE 50 mg/1 mL; PHENYLEPHRINE HYDROCHLORIDE 2.5 mg/1 mL
INACTIVE INGREDIENTS: ARGININE; SODIUM BENZOATE; ETHOXYDIGLYCOL; EDETATE DISODIUM ANHYDROUS; ANHYDROUS CITRIC ACID; BENZYL ALCOHOL; DIETHYLENE GLYCOL MONOETHYL ETHER ACETATE; HAMAMELIS VIRGINIANA (WITCH HAZEL) LEAF WATER; POLYSORBATE 20; WATER; SODIUM SULFITE; ALOE BARBADENSIS LEAF JUICE; MATRICARIA CHAMOMILLA FLOWERING TOP; PHENOXYETHANOL; ALLANTOIN

Active Ingredients Purpose

Lidocaine 5% ………………………………………….Local Anesthetic

Phenylephrine HCl 0.25% ………………………….....Vasoconstrictor

Uses

■ For the temporary relief of local and anorectal itching and discomfort associated with anorectal disorders and anorectal inflammation.

■ For the temporary relief of pain, burning and soreness.

■ Temporarily shrinks hemorrhoidal tissue.

■ Temporarily reduces the swelling associated with irritation in hemorrhoids and other anorectal disorders.

Warnings

■ If condition worsens or does not improve within 7 days, consult a doctor.

■ Do not exceed the recommended daily dosage unless directed by a doctor.

■ In case of bleeding, consult a doctor promptly.

■ Do not put this product into the rectum by using fingers or any mechanical device or applicator.

■ Certain persons can develop allergic reactions to ingredients in this product. If the symptom being treated does not subside or if redness, irritation, swelling, pain, or other symptoms develop or increase, discontinue use and consult a doctor.

■ Do not use this product if you have heart disease, high blood pressure, thyroid disease, diabetes, or difficulty in urination due to enlargement of the prostate gland unless directed by a doctor.

■ Ask a doctor or pharmacist before use if you are presently taking a prescription drug for high blood pressure or depression.

Directions

■ Adults: When practical, cleanse the affected area with mild soap and warm water and rinse thoroughly. Gently dry by patting or blotting with toilet tissue or a soft cloth before application of this product. Children under 12 years of age: consult a doctor.

■ Apply externally to the affected area up to 4 times daily.

Other Information

■ Keep away from direct sunlight or heat.

■ Store at room temperature 15°-30°C (59°-86°F).

■ This package is child-resistant. Keep out of reach of children.

■ In case of accidental overdose or ingestion, call a doctor or poison control center immediately.

■ Do not use this product if seal is broken or missing.

Inactive Ingredients

Alcohol, Allantoin, Aloe Barbadensis Leaf Juice, Arginine Hydrochloride, Benzyl Alcohol, Chamomilla Recutita (Matricaria) Flower Extract, Citric Acid, Disodium EDTA, Ethoxydiglycol, Glycerin, Hamamelis Virginiana (Witch Hazel) Water, Polysorbate 20, Propylene Glycol, Sodium Benzoate, Sodium Chloride, Sodium Citrate, Sodium Hydroxide, Sodium Metabisulfite, Sodium Sulfite, Water

Purpose………………………………………….Local Anesthetic

PACKAGE LABEL

NUMB520

SPRAY

5% Lidocaine

0.25% Phenylephrine HCl

CHILD-RESISTANT PACKAGING

Topical Anorectal Spray

2.4 fl.oz e 72 mL